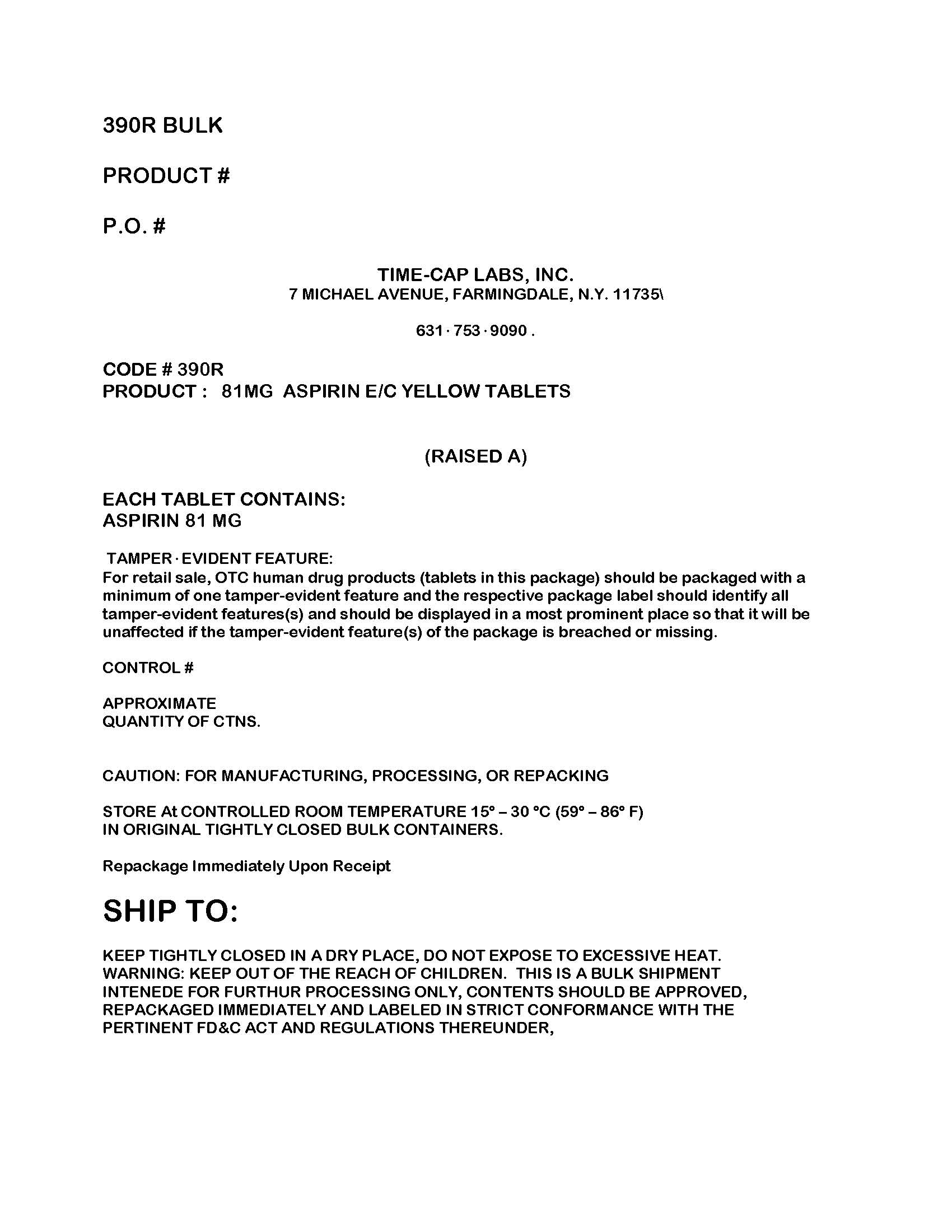 DRUG LABEL: aspirin
NDC: 49483-390 | Form: TABLET
Manufacturer: Time-Cap Labs, Inc
Category: otc | Type: HUMAN OTC DRUG LABEL
Date: 20181217

ACTIVE INGREDIENTS: ASPIRIN 81 mg/1 1
INACTIVE INGREDIENTS: ANHYDROUS LACTOSE; POLYSORBATE 80; DIMETHICONE; CROSCARMELLOSE SODIUM; FERRIC OXIDE YELLOW; D&C YELLOW NO. 10; CARNAUBA WAX; SILICON DIOXIDE; MICROCRYSTALLINE CELLULOSE; METHACRYLIC ACID - METHYL METHACRYLATE COPOLYMER (1:1); SODIUM HYDROXIDE; SODIUM LAURYL SULFATE; TALC; TITANIUM DIOXIDE; TRIETHYL CITRATE

49483-390 ASA 81 MG

Active ingredient (in each tablet)
Aspirin 81 mg (NSAID*). . . . . . . . . . . . . . . . . . .Pain reliever
*nonsteroidal anti-inflammatory drug

INACTIVE INGREDIENT

anhydrous lactose, carnauba wax, colloidal silicon dioxide, croscarmellose sodium, d&c yellow#10 aluminum lake, iron oxide ochre, methacrylic acid and ethyl acrylate copolymer, microcrystalline cellulose, Polysorbate 80, simethicone, sodium hydroxide, sodium lauryl sulfate, talc, titanium dioxide, triethyl citrate

PURPOSE

Uses • temporarily relieves minor aches and pains
• for other uses, see your doctor, but do not use for more
than 10 days without consulting your doctor because
serious side effects may occur

Directions

drink a full glass of water with each dose
adults and children 12 years and over: take 4 to 8 tablets every 4 hours not to exceed 48 tablets in 24 hours unless directed by a doctor
children under 12 years: consult a doctor

Ask a doctor before use if • stomach bleeding warning
applies to you • you have a history of stomach
problems, such as heartburn • you have high blood
pressure, heart disease, liver cirrhosis, or kidney disease
• you are taking a diuretic • you have asthma • you
have not been drinking fluids • you have lost a lot of
fluid due to vomiting or diarrhea
Ask a doctor or pharmacist before use if you are
• taking a prescription drug for diabetes, gout, or arthritis
• under a doctor’s care for any serious condition
• taking any other drug

Ask a doctor or pharmacist before use if you are
• taking a prescription drug for diabetes, gout, or arthritis
• under a doctor’s care for any serious condition
• taking any other drug

PREGNANCY OR BREAST FEEDING

If pregnant or breast-feeding, ask a health professional before
use. It is especially important not to use aspirin during the last
3 months of pregnancy unless definitely directed to do so by a
doctor because it may cause problems in the unborn child or
complications during delivery.
Keep out of reach of children. In case of overdose, get medical
help or contact a Poison Control Center right away.

Keep out of reach of children. In case of overdose, get medical help or contact a Poison Control Center right away.

Uses

temporarily relieves minor aches and pains
for other uses, see your doctor, but do not use for more than 10 days without consulting your doctor because serious side effects may occur

Warnings
Reye's syndrome: Children and teenagers who have or are recovering from chicken pox or flu-like symptoms should not use this product. When using this product, if changes in behavior with nausea and vomiting occur, consult a doctor because these symptoms could be an early sign of Reye's syndrome, a rare but serious illness.
Allergy alert: Aspirin may cause a severe allergic reaction, which may include:

hives
facial swelling
shock
asthma (wheezing)

Stomach bleeding warning: This product contains an NSAID, which may cause severe stomach bleeding. The chance is higher if you:

are age 60 or older
have had stomach ulcers or bleeding problems
take a blood thinning (anticoagulant) or steroid drug
have 3 or more alcoholic drinks every day while using this product
take more or for a longer time than directed
take other drugs containing prescription or nonprescription NSAIDs (aspirin, ibuprofen, naproxen, or others)

PACKAGE LABEL

Enter section text here